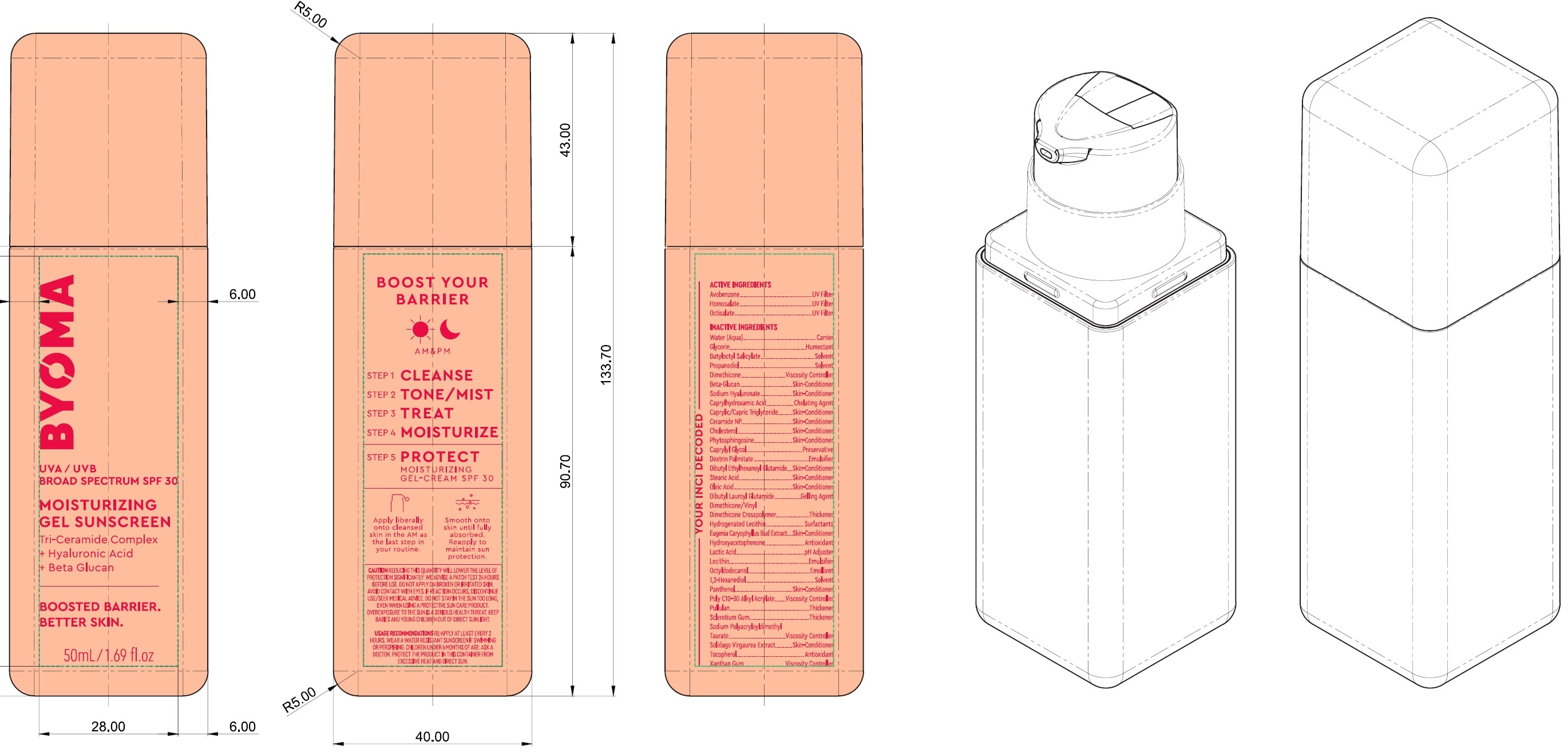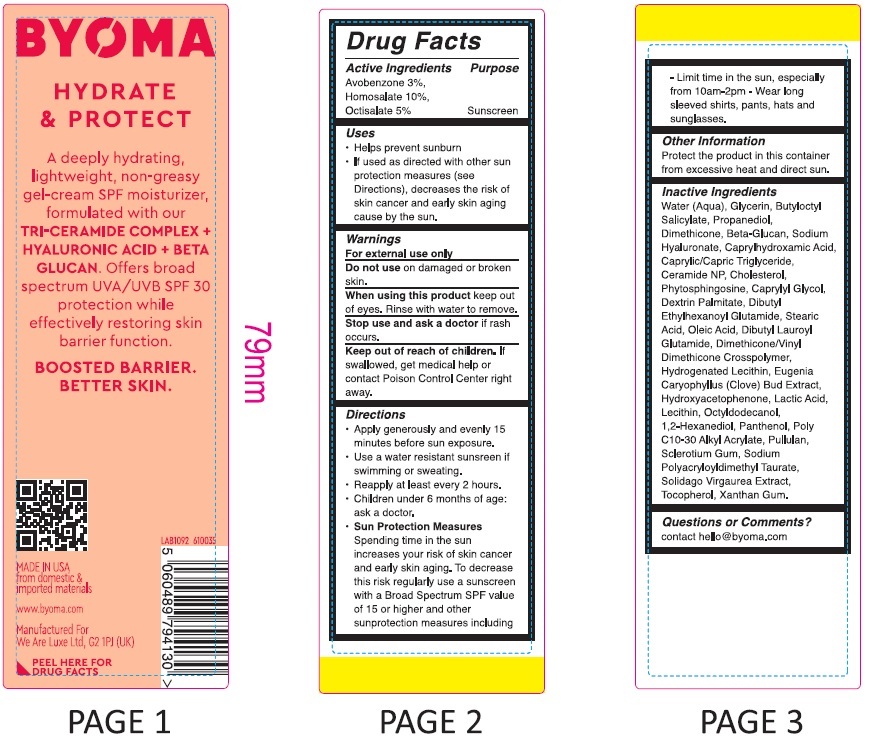 DRUG LABEL: Byoma Moisturizing Gel Sunscreen Broad Spectrum SPF 30
NDC: 14268-123 | Form: CREAM
Manufacturer: ENGLEWOOD LAB, INC.
Category: otc | Type: HUMAN OTC DRUG LABEL
Date: 20231212

ACTIVE INGREDIENTS: AVOBENZONE 30 mg/1 mL; HOMOSALATE 100 mg/1 mL; OCTISALATE 50 mg/1 mL
INACTIVE INGREDIENTS: WATER; GLYCERIN; BUTYLOCTYL SALICYLATE; PROPANEDIOL; DIMETHICONE; HYALURONATE SODIUM; CAPRYLHYDROXAMIC ACID; MEDIUM-CHAIN TRIGLYCERIDES; CERAMIDE NP; CHOLESTEROL; PHYTOSPHINGOSINE; CAPRYLYL GLYCOL; DIBUTYL ETHYLHEXANOYL GLUTAMIDE; STEARIC ACID; OLEIC ACID; DIBUTYL LAUROYL GLUTAMIDE; CLOVE; HYDROXYACETOPHENONE; LACTIC ACID; OCTYLDODECANOL; 1,2-HEXANEDIOL; PANTHENOL; PULLULAN; BETASIZOFIRAN; TOCOPHEROL; XANTHAN GUM

Byoma Moisturizing Gel Sunscreen Broad Spectrum SPF 30

Active Ingredients

Avobenzone 3%,

Homosalate 10%,

Octisalate 5%

Purpose

Sunscreen

Uses

- Helps prevent sunburn
- if used as directed with other sun protection measures (see Directions), decreases the risk of skin cancer and early skin aging caused by the sun.

Warnings

For external use only

Do not use

on damaged or broken skin

When using this product

keep out of eyes. Rinse with water to remove.

Stop use and ask a doctor if

rash occurs.

Keep out of reach of children.

If swallowed, get medical help or contact a Poison Control Center right away.

Directions

• Apply generously and evenly 15 minutes before sun exposure. • Use a water resistant sunscreen if swimming or sweating: • Reapply at least every 2 hours. • Children under 6 months of age: ask a doctor. • Spending time in the sun increases your risk of skin cancer and early skin aging. To decrease this risk regularly use a sunscreen with a Broad Spectrum SPF value of 15 or higher and other sunprotection measures including • Limit time in the sun, especially from 10 a.m.– 2 p.m - Wear long sleeved shirts, pants, hats and sunglasses.
Sun Protection Measures

Other information

Protect the product in this container from excessive heat and direct sun.

Inactive Ingredients

Water (Aqua), Glycerin, Butyloctyl Salicylate, Propanediol, Dimethicone, Beta-Glucan, Sodium Hyaluronate, Caprylhydroxamic Acid, Caprylic/Capric Trilgyceride, Ceramide NP, Cholesterol, Phytosphingosine, Caprylyl Glycol, Dextrin Palmitate, Dibutyl Ethylhexanoyl Glutamide, Stearic Acid, Oleic Acid, DIbutyl Lauroyl Glutamide, Dimethicone/Vinyl Dimethicone Crosspolymer, Hydrogenated Lecithin, Eugenia Caryophyllus (Clove) Bud Extract, Hydroxyacetophenone, Lactic Acid, Lecithin, Octyldodecanol, 1,2-Hexanediol, Panthenol, Poly C10-30 Alkyl Acrylate, Pullulan, Sclerotium Gum, Sodium Polyacryloyldimethyl Taurate, Solidago Virgaurea Extract, Tocopherol, Xanthan Gum.

Questions or Comments?

contact hello@byoma.com